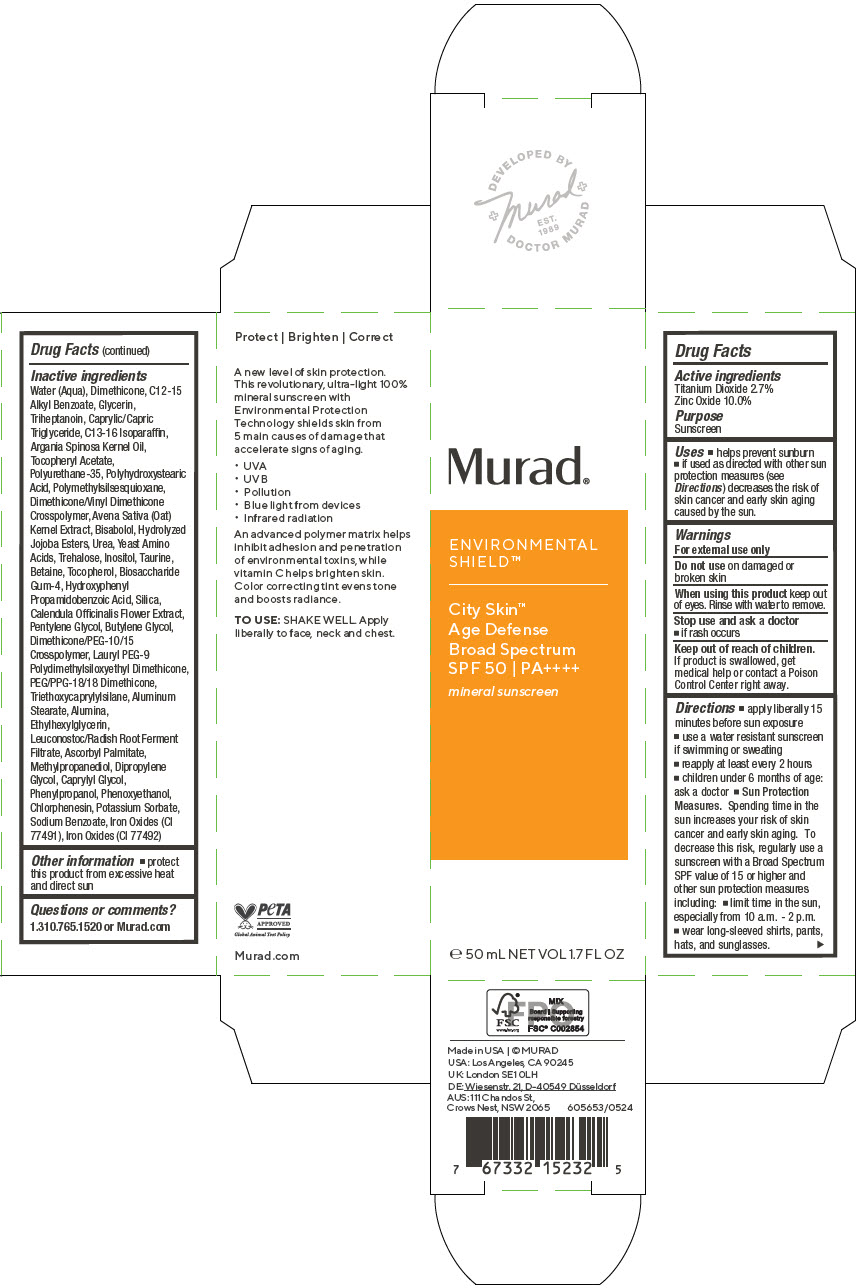 DRUG LABEL: City Skin Age Defense Broad Spectrum
NDC: 70381-127 | Form: LOTION
Manufacturer: Murad, LLC
Category: otc | Type: HUMAN OTC DRUG LABEL
Date: 20250328

ACTIVE INGREDIENTS: TITANIUM DIOXIDE 2.7 g/100 mL; ZINC OXIDE 10 g/100 mL
INACTIVE INGREDIENTS: WATER; DIMETHICONE; ALKYL (C12-15) BENZOATE; GLYCERIN; TRIHEPTANOIN; MEDIUM-CHAIN TRIGLYCERIDES; C13-16 ISOPARAFFIN; ARGAN OIL; .ALPHA.-TOCOPHEROL ACETATE; POLYURETHANE-35 (NOT MORE THAN 500 MPA.S AT 40%); POLYHYDROXYSTEARIC ACID (2300 MW); POLYMETHYLSILSESQUIOXANE (4.5 MICRONS); DIMETHICONE/VINYL DIMETHICONE CROSSPOLYMER (SOFT PARTICLE); OAT; LEVOMENOL; HYDROLYZED JOJOBA ESTERS (ACID FORM); UREA; AMINO ACIDS, SOURCE UNSPECIFIED; TREHALOSE; INOSITOL; TAURINE; BETAINE; TOCOPHEROL; BIOSACCHARIDE GUM-4; HYDROXYPHENYL PROPAMIDOBENZOIC ACID; SILICON DIOXIDE; CALENDULA OFFICINALIS FLOWER; PENTYLENE GLYCOL; BUTYLENE GLYCOL; DIMETHICONE/PEG-10/15 CROSSPOLYMER; LAURYL PEG-9 POLYDIMETHYLSILOXYETHYL DIMETHICONE; PEG/PPG-18/18 DIMETHICONE; TRIETHOXYCAPRYLYLSILANE; ALUMINUM STEARATE; ALUMINUM OXIDE; ETHYLHEXYLGLYCERIN; LEUCONOSTOC/RADISH ROOT FERMENT FILTRATE; ASCORBYL PALMITATE; METHYLPROPANEDIOL; DIPROPYLENE GLYCOL; CAPRYLYL GLYCOL; PHENYLPROPANOL; PHENOXYETHANOL; CHLORPHENESIN; POTASSIUM SORBATE; SODIUM BENZOATE; FERRIC OXIDE RED; FERRIC OXIDE YELLOW

City Skin Age Defense Broad Spectrum
SPF 50

Drug Facts

ACTIVE INGREDIENT

Active ingredients | Purpose
Titanium Dioxide 2.7% | Sunscreen
Zinc Oxide 10.0% | Sunscreen

Uses

- helps prevent sunburn
- if used as directed with other sun protection measures (see Directions) decreases the risk of skin cancer and early skin aging caused by the sun

Warnings

For external use only

Do not use on damaged or broken skin

When using this product keep out of eyes. Rinse with water to remove.

Stop use and ask a doctor

- if rash occurs

Keep out of reach of children. If product is swallowed, get medical help or contact a Poison Control Center right away.

Directions

- apply liberally 15 minutes before sun exposure
- use a water resistant sunscreen if swimming or sweating
- reapply at least every 2 hours
- children under 6 months of age: ask a doctor
- Sun Protection Measures. Spending time in the sun increases your risk of skin cancer and early skin aging. To decrease this risk, regularly use a sunscreen with a Broad Spectrum SPF value of 15 or higher and other sun protection measures including:
  - limit time in the sun, especially from 10 a.m. - 2 p.m.
  - wear long-sleeved shirts, pants, hats, and sunglasses.

Inactive ingredients

Water (Aqua), Dimethicone, C12-15 Alkyl Benzoate, Glycerin, Triheptanoin, Caprylic/Capric Triglyceride, C13-16 Isoparaffin, Argania Spinosa Kernel Oil, Tocopheryl Acetate, Polyurethane-35, Polyhydroxystearic Acid, Polymethylsilsesquioxane, Dimethicone/Vinyl Dimethicone Crosspolymer, Avena Sativa (Oat) Kernel Extract, Bisabolol, Hydrolyzed Jojoba Esters, Urea, Yeast Amino Acids, Trehalose, Inositol, Taurine, Betaine, Tocopherol, Biosaccharide Gum-4, Hydroxyphenyl Propamidobenzoic Acid, Silica, Calendula Officinalis Flower Extract, Pentylene Glycol, Butylene Glycol, Dimethicone/PEG-10/15 Crosspolymer, Lauryl PEG-9 Polydimethylsiloxyethyl Dimethicone, PEG/PPG-18/18 Dimethicone, Triethoxycaprylylsilane, Aluminum Stearate, Alumina, Ethylhexylglycerin, Leuconostoc/Radish Root Ferment Filtrate, Ascorbyl Palmitate, Methylpropanediol, Dipropylene Glycol, Caprylyl Glycol, Phenylpropanol, Phenoxyethanol, Chlorphenesin, Potassium Sorbate, Sodium Benzoate, Iron Oxides (CI 77491), Iron Oxides (CI 77492)

Other information

- protect this product from excessive heat and direct sun

Questions or comments?

1.310.765.1520 or Murad.com

PRINCIPAL DISPLAY PANEL - 50 mL Bottle Carton

Murad®

ENVIRONMENTAL
SHIELD™

City Skin™
Age Defense
Broad Spectrum
SPF 50 | PA++++

mineral sunscreen

℮ 50 mL NET VOL 1.7 FL OZ